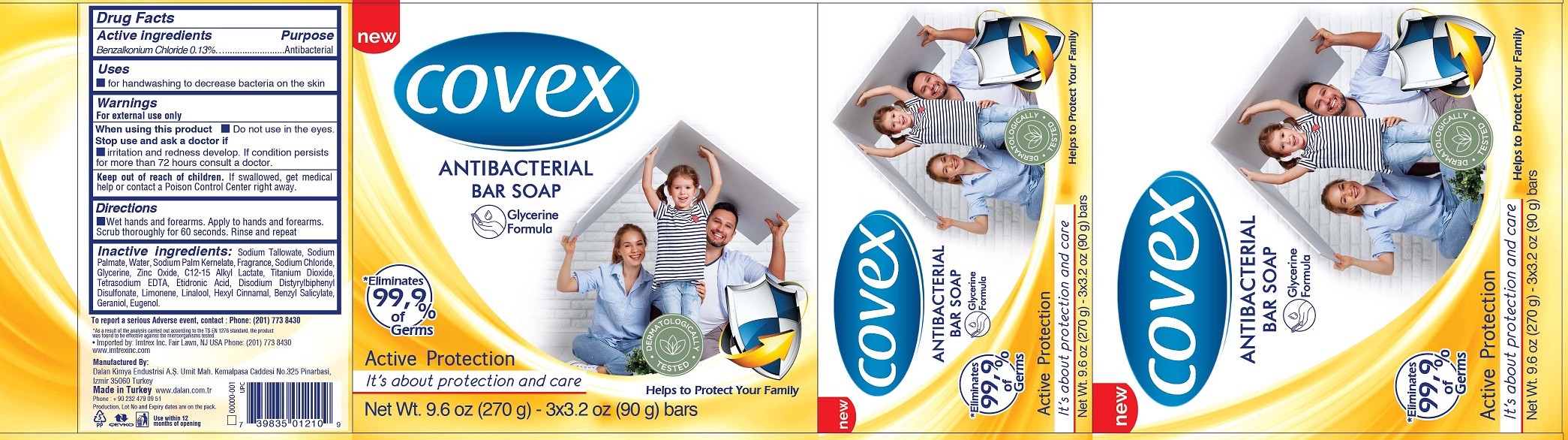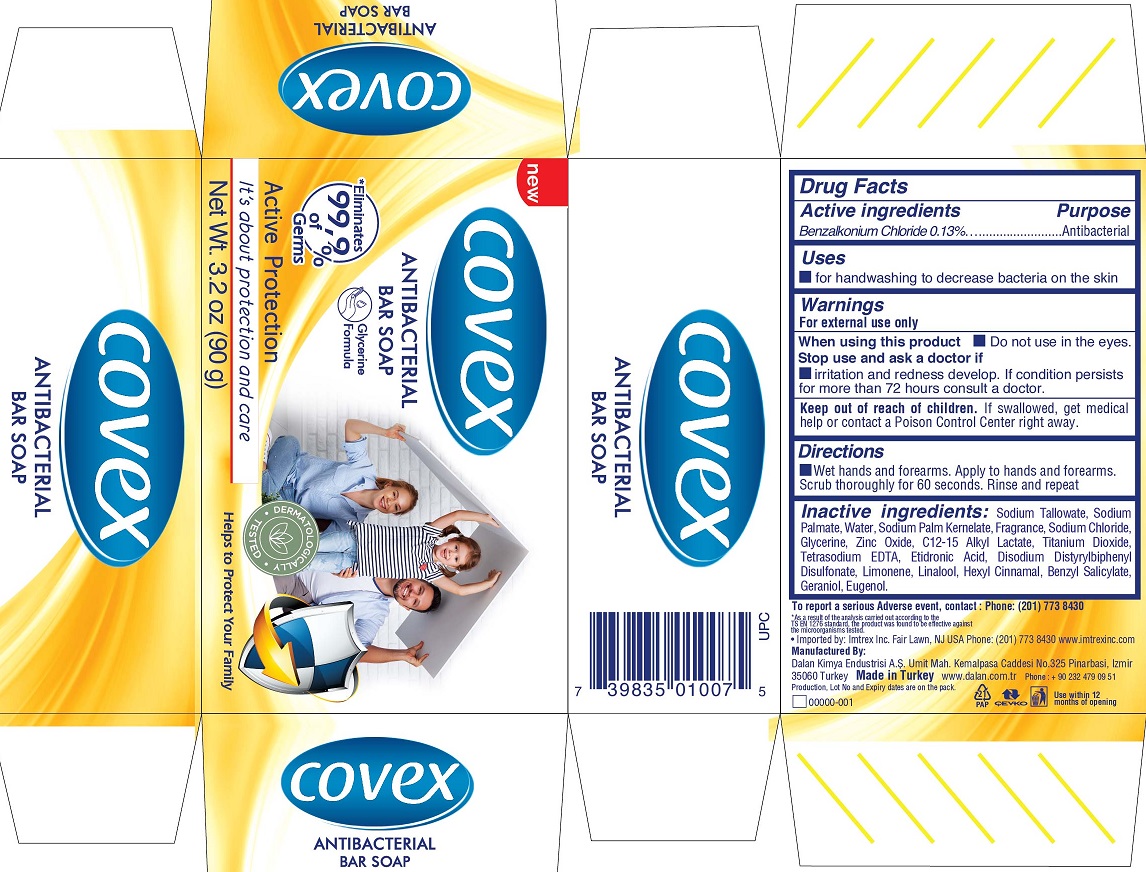 DRUG LABEL: Covex Antibacterial Bar Active Protection
NDC: 51209-021 | Form: SOAP
Manufacturer: DALAN KIMYA ENDUSTRI ANONIM SIRKETI
Category: otc | Type: HUMAN OTC DRUG LABEL
Date: 20260122

ACTIVE INGREDIENTS: BENZALKONIUM CHLORIDE 1.3 mg/1 g
INACTIVE INGREDIENTS: SODIUM TALLOWATE, BEEF; SODIUM PALMATE; WATER; SODIUM PALM KERNELATE; SODIUM CHLORIDE; GLYCERIN; ZINC OXIDE; C12-15 ALKYL LACTATE; TITANIUM DIOXIDE; EDETATE SODIUM; ETIDRONIC ACID; DISODIUM DISTYRYLBIPHENYL DISULFONATE; LIMONENE, (+)-; LINALOOL, (+/-)-; .ALPHA.-HEXYLCINNAMALDEHYDE; BENZYL SALICYLATE; GERANIOL; EUGENOL

Covex Antibacterial Bar Soap Active Protection

Active ingredients

Benzalkonium Chloride 0.13%

Purpose

Antibacterial

Uses

for handwashing to decrease bacteria on the skin

Warnings

For external use only

Do not use

- in the eyes.

Stop use and ask a doctor if

irritation and redness develop. If condition persists for more than 72 hours consult a doctor.

Keep out of reach of children.

If swallowed, get medical help or contact a Poison Control Center right away.

Directions

Wet hands and forearms. Apply to hands and forearms. Scrub thoroughly for 60 seconds. Rinse and repeat

Inactive ingredients:

Sodium Tallowate, Sodium Palmate, Water, Sodium Palm Kernelate, Fragrance, Sodium Chloride, Glycerine, Zinc Oxide, C12-15 Alkyl Lactate, Titanium Dioxide, Tetrasodium EDTA, Etidronic Acid, Disodium Distyrylbiphenyl Disulfonate, Limonene, Linalool, Hexyl Cinnamal, Benzyl Salicylate, Geraniol, Eugenol.